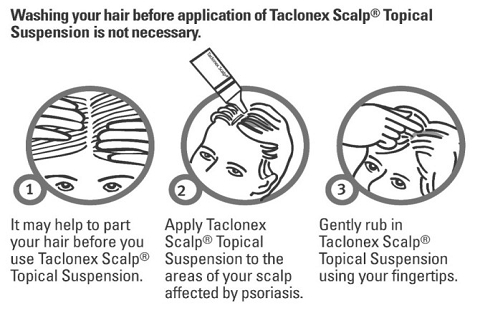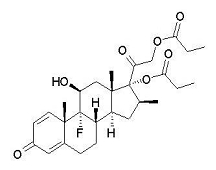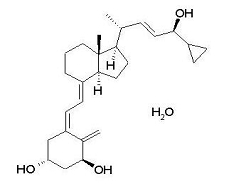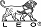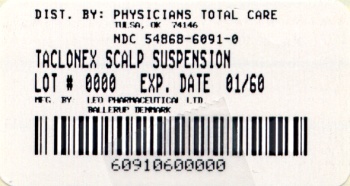 DRUG LABEL: Taclonex Scalp
NDC: 54868-6091 | Form: SUSPENSION
Manufacturer: Physicians Total Care, Inc.
Category: prescription | Type: HUMAN PRESCRIPTION DRUG LABEL
Date: 20100818

ACTIVE INGREDIENTS: CALCIPOTRIENE 50 ug/1 g; BETAMETHASONE DIPROPIONATE 0.643 mg/1 g
INACTIVE INGREDIENTS: HYDROGENATED CASTOR OIL; MINERAL OIL

HIGHLIGHTS OF PRESCRIBING INFORMATION

These highlights do not include all the information needed to use Taclonex Scalp® Topical Suspension safely and effectively. See full prescribing information for Taclonex Scalp® Topical Suspension. Initial U.S. Approval: 2006

1 INDICATIONS AND USAGE

Taclonex Scalp® Topical Suspension is a vitamin D analog and corticosteroid combination product indicated for the topical treatment of moderate to severe psoriasis vulgaris of the scalp in adults 18 years and older (1.1)

Limitations of Use:

• Do not use on the face, axillae or groin (1.2)

• Do no use if atrophy is present at the treatment site (1.2)

2 DOSAGE AND ADMINISTRATION

Apply Taclonex Scalp® Topical Suspension to affected areas on the scalp once daily for 2 weeks or until cleared. Treatment may be continued for up to 8 weeks (2.1). The maximum weekly dose should not exceed 100 g (1.2). Shake before use (2).

Taclonex Scalp® Topical Suspension is not for oral, ophthalmic, or intravaginal use.

3 DOSAGE FORMS AND STRENGTHS

Suspension.

Each gram of Taclonex Scalp® Topical Suspension contains 52.18 mcg of calcipotriene hydrate (equivalent to 50 mcg of calcipotriene) and 0.643 mg of betamethasone dipropionate (equivalent to 0.5 mg of betamethasone) (3)

4 CONTRAINDICATIONS

None (4)

5 WARNINGS AND PRECAUTIONS

- Hypercalcemia and hypercalciuria have been reported. If either occurs, discontinue until parameters of calcium metabolism normalize (5.1)
- Topical corticosteroids can produce reversible HPA axis suppression, Cushing's syndrome and unmask latent diabetes (5.2)
- Rate of adrenal suppression increased with treatment duration (5.2)
- Systemic absorption may require evaluation for hypothalamic-pituitary-adrenal (HPA) axis suppression (5.2)
- Modify use should HPA axis suppression develop (5.2)
- Potent corticosteroids, use on large areas, prolonged use or occlusive use may increase systemic absorption (5.1)
- Local adverse reactions may include atrophy, striae, irritation, acneiform eruptions, hypopigmentation, and allergic contact dermatitis and may be more likely with occlusive use or more potent corticosteroids (5.3, 6.1)
- Children may be more susceptible to systemic toxicity when treated with topical corticosteroids (5.2, 8.4)

6 ADVERSE REACTIONS

The most common adverse reactions (≥ 1%) are folliculitis and burning sensation of skin (6.1)

To report SUSPECTED ADVERSE REACTIONS, contact LEO Pharma Inc at Phone 1-8877-494-4536 or FDA at 1-800-FDA-1088 or www.fda.gov/medwatch.

FULL PRESCRIBING INFORMATION

1 INDICATIONS AND USAGE

Enter section text here

1.1 Indication

Taclonex Scalp® Topical Suspension is indicated for the topical treatment of moderate to severe psoriasis vulgaris of the scalp in adults 18 years and older.

1.2 Limitations of Use

- Taclonex Scalp® Topical Suspension should not be used on the face, axillae or groin
- Taclonex Scalp® Topical Suspension should not be used if there is atrophy at the treatment site

2 DOSAGE AND ADMINISTRATION

Enter section text here

2.1 Usual Dosage and Administration

Apply Taclonex Scalp® Topical Suspension to affected areas on the scalp once daily for 2 weeks or until cleared. Treatment may be continued for up to 8 weeks. The maximum weekly dose should not exceed 100 g. Patients should shake the bottle prior to using the product. Patients should wash their hands after applying Taclonex Scalp® Topical Suspension.

Taclonex Scalp® Topical Suspension is not for oral, ophthalmic, or intravaginal use.

3 DOSAGE FORMS AND STRENGTHS

Suspension.

Each gram of Taclonex Scalp® Topical Suspension contains 52.18 mcg of calcipotriene hydrate (equivalent to 50 mcg of calcipotriene) and 0.643 mg of betamethasone dipropionate (equivalent to 0.5 mg of betamethasone).

4 CONTRAINDICATIONS

None.

5 WARNINGS AND PRECAUTIONS

Enter section text here

5.1 Effects on Calcium Metabolism

Hypercalcemia and hypercalciuria have been observed with use of Taclonex Scalp® Topical Suspension. If hypercalcemia or hypercalciuria develop, treatment should be discontinued until parameters of calcium metabolism have normalized. The effects of Taclonex Scalp® Topical Suspension on calcium metabolism following treatment durations of more than 8 weeks have not been evaluated.

5.2 Effects on Endocrine System

Systemic absorption of topical corticosteroids can produce reversible hypothalamic-pituitary-adrenal (HPA) axis suppression with the potential for clinical glucocorticosteroid insufficiency. This may occur during treatment or upon withdrawal of the topical corticosteroid.

In a study of 32 subjects treated with Taclonex Scalp® Topical Suspension on the scalp and Taclonex® Ointment on the body, adrenal suppression was identified in 5 of 32 subjects (15.6%) after 4 weeks of treatment and in 2 of 11 subjects (18.2%) who continued treatment for 8 weeks. [See CLINICAL PHARMACOLOGY Pharmacodynamics (12.2)]

Because of the potential for systemic absorption, use of topical corticosteroids may require that patients be periodically evaluated for HPA axis suppression. Factors that predispose a patient using a topical corticosteroid to HPA axis suppression include the use of more potent steroids, use over large surface areas, use over prolonged periods, use under occlusion, use on an altered skin barrier, and use in patients with liver failure.

An ACTH stimulation test may be helpful in evaluating patients for HPA axis suppression. If HPA axis suppression is documented, an attempt should be made to gradually withdraw the drug, to reduce the frequency of application, or to substitute a less potent steroid. Manifestations of adrenal insufficiency may require supplemental systemic corticosteroids. Recovery of HPA axis function is generally prompt and complete upon discontinuation of topical corticosteroids.

Cushing’s syndrome, hyperglycemia, and unmasking of latent diabetes mellitus can also result from systemic absorption of topical corticosteroids.

Use of more than one corticosteroid-containing product at the same time may increase the total systemic corticosteroid exposure.

Pediatric patients may be more susceptible to systemic toxicity from use of topical corticosteroids. [See Use in Specific Populations (8.4)]

5.3 Local Adverse Reactions with Topical Corticosteroids

Local adverse reactions may be more likely to occur with occlusive use, prolonged use or use of higher potency corticosteroids. Reactions may include atrophy, striae, telangiectasias, burning, itching, irritation, dryness, folliculitis, acneiform eruptions, hypopigmentation, perioral dermatitis, allergic contact dermatitis, secondary infection, and miliaria. Some local adverse reactions may be irreversible.

5.4 Allergic Contact Dermatitis with Topical Corticosteroids

Allergic contact dermatitis to any component of topical corticosteroids is usually diagnosed by a failure to heal rather than a clinical exacerbation. Clinical diagnosis of allergic contact dermatitis can be confirmed by patch testing.

5.5 Allergic Contact Dermatitis with Topical Calcipotriene

Allergic contact dermatitis has been observed with use of topical calcipotriene. Clinical diagnosis of allergic contact dermatitis can be confirmed by patch testing.

5.6 Concomitant Skin Infections

Concomitant skin infections should be treated with an appropriate antimicrobial agent. If the infection persists, Taclonex Scalp® Topical Suspension should be discontinued until the infection has been adequately treated.

5.7 Unevaluated Uses

The safety and efficacy of Taclonex Scalp® Topical Suspension in patients with known or suspected disorders of calcium metabolism have not been evaluated.

The safety and efficacy of Taclonex Scalp® Topical Suspension in patients with erythrodermic, exfoliative or pustular psoriasis have not been evaluated.

The safety and efficacy of Taclonex Scalp® Topical Suspension in patients with severe renal insufficiency or severe hepatic disorders have not been evaluated.

5.8 Eye Exposures

Avoid eye exposures. Taclonex Scalp® Topical Suspension may cause eye irritation.

5.9 Ultraviolet Light Exposures

Patients who apply Taclonex Scalp® Topical Suspension to exposed skin (e.g. a bald scalp) should avoid excessive exposure to either natural or artificial sunlight, including tanning booths, sun lamps, etc. Physicians may wish to limit or avoid use of phototherapy to the scalp in patients who use Taclonex Scalp® Topical Suspension.

6 ADVERSE REACTIONS

Because clinical trials are conducted under widely varying conditions, adverse reaction rates observed in the clinical trials of a drug cannot be directly compared to rates in the clinical trials of another drug and may not reflect the rates observed in practice.

6.1 Clinical Studies Experience

The rates of adverse reactions given below were derived from randomized, multicenter, prospective vehicle- and/or active-controlled clinical studies in subjects with scalp psoriasis. Subjects applied study product once daily for 8 weeks, and the median weekly

dose was 12.6 g.

Adverse reactions that occurred in ≥ 1% of subjects treated with Taclonex Scalp® Topical Suspension and at a rate higher than in subjects treated with vehicle are presented in Table 1:

Table 1
Number and Percentage of Patients with Adverse Reactions in Scalp
Psoriasis Studies
(Events Reported by ≥ 1% of Subjects and for Which a Relationship is Possible)
 | Taclonex Scalp® Topical Suspension N=1,953 | Betamethasone dipropionate in vehicle; N=1,214 | Calcipotriene in vehicle N=979 | Vehicle; N=173
Event | # of subjects (%)
Folliculitis | 16 (1%) | 12 (1%) | 5 (1%) | 0 (0%)
Burning sensation of skin | 13 (1%) | 10 (1%) | 29 (3%) | 0 (0.0%)

Other less common reactions (less than 1% but more than 0.1%) were, in decreasing order of incidence: acne, exacerbation of psoriasis, eye irritation, and pustular rash.

In a 52-week study, adverse reactions that were reported by greater than 1% of subjects treated with Taclonex Scalp® Topical Suspension were pruritus (3.6%), psoriasis (2.4%), erythema (2.1%), skin irritation (1.4%), and folliculitis (1.2%). The effects of Taclonex Scalp® Topical Suspension on calcium metabolism and the HPA axis were not investigated in the 52-week study.

8 USE IN SPECIFIC POPULATIONS

Enter section text here

8.1 Pregnancy

Teratogenic Effects: Pregnancy Category C

Animal reproduction studies have not been conducted with Taclonex Scalp® Topical Suspension. Taclonex Scalp® Topical Suspension contains calcipotriene that has been shown to be fetotoxic and betamethasone dipropionate that has been shown to be teratogenic in animals when given systemically. There are no adequate and well-controlled studies in pregnant women. Taclonex Scalp® Topical Suspension should be used during pregnancy only if the potential benefit to the patient justifies the potential risk to the fetus.

Teratogenicity studies with calcipotriene were performed by the oral route in rats and rabbits. In rabbits, increased maternal and fetal toxicity were noted at a dosage of 12 mcg/kg/day (144 mcg/m^2/day); a dosage of 36 mcg/kg/day (432 mcg/m^2/day) resulted in a significant increase in the incidence of incomplete ossification of the pubic bones and forelimb phalanges of fetuses. In a rat study, a dosage of 54 mcg/kg/day (324 mcg/m^2/day) resulted in a significantly increased incidence of skeletal abnormalities (enlarged fontanelles and extra ribs). The enlarged fontanelles were most likely due to the effect of calcipotriene upon calcium metabolism. The estimated maternal and fetal no-adverse effect levels (NOAEL) in the rat (108 mcg/m^2/day) and rabbit (48 mcg/m^2/day) derived from oral studies are lower than the maximum topical dose of calcipotriene in man (460 mcg/m^2/day).

Corticosteroids are generally teratogenic in laboratory animals when administered systemically at relatively low dosage levels. Betamethasone dipropionate has been shown to be teratogenic in mice and rabbits when given by the subcutaneous route at doses of 156 mcg/kg (468 mcg/m^2/day) and 2.5 mcg/kg (30 mcg/m^2/day), respectively. Those dose levels are lower than the maximum topical dose in man (about 5,950 mcg/m^2/day). The abnormalities observed included umbilical hernia, exencephaly and cleft palate.

Pregnant women were excluded from the clinical studies conducted with Taclonex Scalp® Topical Suspension.

8.3 Nursing Mothers

Systemically administered corticosteroids appear in human milk and could suppress growth, interfere with endogenous corticosteroid production, or cause other untoward effects.

It is not known whether topically administered calcipotriene or corticosteroids could result in sufficient systemic absorption to produce detectable quantities in human milk.

Because many drugs are excreted in human milk, caution should be exercised when Taclonex Scalp® Topical Suspension is administered to a nursing woman.

8.4 Pediatric Use

Safety and effectiveness of the use of Taclonex Scalp® Topical Suspension in pediatric patients have not been studied. Because of a higher ratio of skin surface area to body mass, children under the age of 12 years may be at particular risk of systemic adverse effects when they are treated with topical corticosteroids. [See Warnings and Precautions (5.2)]

HPA axis suppression, Cushing’s syndrome, linear growth retardation, delayed weight gain, and intracranial hypertension have been reported in children receiving topical corticosteroids. Manifestations of adrenal suppression in children include low plasma cortisol levels and absence of response to ACTH stimulation. Manifestations of intracranial hypertension include bulging fontanelles, headaches, and bilateral papilledema.

8.5 Geriatric Use

Of the total number of patients in the controlled clinical studies of Taclonex Scalp® Topical Suspension, 334 were 65 years or older, while 84 were 75 years or older.

No overall differences in safety or effectiveness of Taclonex Scalp® Topical Suspension were observed between these patients and younger patients. All other reported clinical experience has not identified any differences in response between elderly and younger

patients.

10 OVERDOSAGE

Taclonex Scalp® Topical Suspension can be absorbed in sufficient amounts to produce systemic effects [See WARNINGS AND PRECAUTIONS (5.1)].

11 DESCRIPTION

Taclonex Scalp® Topical Suspension contains calcipotriene hydrate and betamethasone dipropionate. It is intended for topical use on the scalp.

Calcipotriene hydrate is a synthetic vitamin D3 analogue.

Chemically, calcipotriene hydrate is 9,10-Secochola-5,7,10(19),22- tetraene-1,3,24-triol,24-cyclo-propyl-, monohydrate, (1α,3ß,5Z,7E,22E,24S) with the empirical formula C27H40O3,H2O, a molecular weight of 430.6, and the following structural formula:

Calcipotriene hydrate is a white to almost white, crystalline compound.

Betamethasone dipropionate is a synthetic corticosteroid.

Betamethasone dipropionate has the chemical name Pregna-1,4- diene-3,20-dione-9-fluoro-11-hydroxy-16-methyl-17,21-bis(1-oxypropoxy)-(11ß,16ß), with the empirical formula C28H37FO7, a molecular weight of 504.6, and the following structural formula:

Betamethasone dipropionate is a white to almost white, crystalline powder.

Each gram of Taclonex Scalp® Topical Suspension contains 52.18 mcg of calcipotriene hydrate (equivalent to 50 mcg of calcipotriene) and 0.643 mg of betamethasone dipropionate (equivalent to 0.5 mg of betamethasone) in a base of hydrogenated castor oil, PPG-15 stearyl ether and mineral oil.

12 CLINICAL PHARMACOLOGY

Enter section text here

12.1 Mechanism of Action

Taclonex Scalp® Topical Suspension combines the pharmacological effects of calcipotriene hydrate as a synthetic vitamin D3 analogue and betamethasone dipropionate as a synthetic corticosteroid. However, while their pharmacologic and clinical effects are known, the exact mechanisms of their actions in psoriasis vulgaris are unknown.

12.2 Pharmacodynamics

Hypothalamic-Pituitary-Adrenal (HPA) Axis Suppression:

HPA axis suppression was evaluated in adult subjects (N=32) with extensive psoriasis involving at least 30% of the scalp and, in total, 15-30% of the body surface area. Treatment consisted of once daily application of Taclonex Scalp® Topical Suspension on the scalp in combination with Taclonex® Ointment on the body for 4 to 8 weeks. Adrenal suppression as indicated by a 30-minute post-stimulation cortisol level ≤ 18 mcg/dL was observed in 5 of 32 subjects (15.6%) after 4 weeks of treatment and in 2 of 11 subjects (18.2%) who continued treatment for 8 weeks.

Effects on Calcium Metabolism:

In the study described above, the effects of once daily application of Taclonex Scalp® Topical Suspension on the scalp in combination with Taclonex® Ointment on the body for 4 to 8 weeks on calcium metabolism were also examined. Following once daily application of Taclonex Scalp® Topical Suspension on the scalp in combination with Taclonex® Ointment on the body, elevated urinary calcium levels outside the normal range were observed in two subjects (one at 4 weeks and one at 8 weeks).

12.3 Pharmacokinetics

Absorption

Taclonex Scalp® Topical Suspension:

The systemic effect of Taclonex Scalp® Topical Suspension in extensive psoriasis was investigated in the study described above. In this study, the serum levels of calcipotriene and betamethasone dipropionate and their major metabolites were measured after 4 and 8 weeks of once daily application of Taclonex Scalp® Topical Suspension on the scalp in combination with Taclonex® Ointment on the body. Calcipotriene and betamethasone dipropionate were below the lower limit of quantification in all serum samples of the 34 subjects evaluated.

However, one major metabolite of calcipotriene (MC1080) was quantifiable in 10 of 34 (29.4%) subjects at week 4 and in five of 12 (41.7%) subjects at week 8. The major metabolite of betamethasone dipropionate, betamethasone 17-propionate (B17P) was also quantifiable in 19 of 34 (55.9%) subjects at week 4 and seven of 12 (58.3%) subjects at week 8. The serum concentrations for MC1080 ranged from 20-75 pg/mL. The clinical significance of this finding is unknown.

Metabolism

Calcipotriene:

Calcipotriene metabolism following systemic uptake is rapid and occurs in the liver. The primary metabolites of calcipotriene are less potent than the parent compound.

Calcipotriene is metabolized to MC1046 (the α,ß-unsaturated ketone analog of calcipotriene), which is metabolized further to MC1080 (a saturated ketone analog). MC1080 is the major metabolite in plasma. MC1080 is slowly metabolized to calcitroic acid.

Betamethasone dipropionate:

Betamethasone dipropionate is metabolized to betamethasone 17-propionate and betamethasone, including the 6ß-hydroxy derivatives of those compounds by hydrolysis. Betamethasone 17-propionate (B17P) is the primary metabolite.

13 NONCLINICAL TOXICOLOGY

Enter section text here

13.1 Carcinogenesis, Mutagenesis, Impairment of Fertility

When calcipotriene was applied topically for up to 24 months at dosages of 3, 10 and 30 mcg/kg/day (corresponding to 9, 30 and 90 mcg/m^2/day), no biologically significant changes in tumor incidence were observed when compared to control. In a study in which albino hairless mice were exposed to both ultra-violet radiation (UVR) and topically applied calcipotriene, a reduction in the time required for UVR to induce the formation of skin tumors was observed (statistically significant in males only), suggesting that calcipotriene may enhance the effect of UVR to induce skin tumors.

Long-term animal studies have not been performed to evaluate the carcinogenic potential of betamethasone dipropionate.

Calcipotriene did not elicit any genotoxic effects in the Ames mutagenicity assay, the mouse lymphoma TK locus assay, the human lymphocyte chromosome aberration test, or the mouse micronucleus test.

Betamethasone dipropionate did not elicit any genotoxic effect in the Ames mutagenicity assay, the mouse lymphoma TK locus assay, or in the rat micronucleus test.

Studies in rats at doses of up to 54 mcg/kg/day (324 mcg/m^2/day) of calcipotriene indicated no impairment of fertility or general reproductive performance.

Studies in male rats at oral doses of up to 200 mcg/kg/day (1,200 mcg/m^2/day), and in female rats at oral doses of up to 1,000 mcg/kg/day (6,000 mcg/m^2/day) of betamethasone dipropionate indicated no impairment of fertility.

14 CLINICAL STUDIES

Enter section text here

14.1 Controlled Clinical Studies

Two multicenter, randomized, double-blind studies were conducted. In Study One, 1,407 subjects were randomized to one of four treatment groups: Taclonex Scalp® Topical Suspension, betamethasone dipropionate in the same vehicle, calcipotriene hydrate in the same vehicle, or the vehicle alone. Study Two did not include a vehicle arm; 1,280 subjects were randomized to one of three treatment groups: Taclonex Scalp® Topical Suspension, betamethasone dipropionate in the same vehicle, or calcipotriene hydrate in the same vehicle. Both studies enrolled subjects with moderate to very severe scalp psoriasis. The majority of subjects had disease of moderate severity at baseline. Subjects were treated once daily for 8 weeks.

Efficacy was assessed as the proportion of patients at Week 8 with absent or very mild disease according to an Investigator’s Global Assessment of Disease Severity. "Clear" was defined as no evidence of redness, thickness or scaling. "Almost clear" was defined as an overall clinical picture of lesions with the presence of minimal erythema. Table 2 contains the response rates in each of these two trials.

Table 2
Percentage of Patients with Clear or Almost Clear Disease
According to the Investigator’s Global Assessment of Disease Severity
 | Taclonex Scalp®; Topical; Suspension | Betamethasone dipropionate in vehicle | Calcipotriene in vehicle | Vehicle
Study One; Week 2 | (N = 494); 55.5% | (N = 531); 46.1% | (N = 256); 18.4% | (N = 126); 9.5%
Week 8 | 70.0% | 63.1% | 36.7% | 19.8%
Study Two; Week 2 | (N = 512); 47.1% | (N = 517); 36.4% | (N = 251); 12.7% | -; -
Week 8 | 67.2% | 59.6% | 41.0% | -

16 HOW SUPPLIED/STORAGE AND HANDLING

Enter section text here

16.1 How Supplied

Taclonex Scalp® Topical Suspension is available in bottles of:

60 g (NDC 54868-6091-0)

16.2 Storage

Store between 20-25°C (68-77°F); excursions permitted between 15-30°C (59-86°F).

Do not refrigerate. Keep the bottle in the outer carton when not in use.

The product should be used within three months after it has been opened.

16.3 Handling

Keep out of reach of children.

Shake before use.

Rx only.

17 PATIENT COUNSELING INFORMATION

This information is intended to aid in the safe and effective use of this medication. It is not a disclosure of all possible adverse or intended effects.

Patients using Taclonex Scalp® Topical Suspension should receive the following information and instructions.

17.1 Instructions for Use

This medication is to be used as directed by the physician. It is for external use only. Avoid contact with the face or eyes. As with any topical medication, patients should wash hands after application. This medication should not be used for any disorder other than that for which it has been prescribed. The treated skin area should not be bandaged or otherwise covered as to be occlusive, unless directed by the physician.

17.2 Adverse Reactions

Patients should report any signs of adverse reactions to their physician.

17.3 Concomitant Use of other Corticosteroids

Other products containing calcipotriene or a corticosteroid should not be used with Taclonex Scalp® Topical Suspension without first talking to the physician.

17.4 Excessive Exposure to Light

Patients who use Taclonex Scalp® Topical Suspension should avoid excessive exposure to either natural or artificial sunlight (including tanning booths, sun lamps, etc.). Physicians may wish to limit or avoid use of phototherapy in patients who use Taclonex Scalp® Topical Suspension.

PATIENT INFORMATION

Taclonex Scalp® (pronounced TAK-lo-NEKS skalp)

(calcipotriene, 0.005% and betamethasone dipropionate, 0.064%)

Topical Suspension

Read the Patient Information that comes with Taclonex Scalp® Topical Suspension before you start using it and each time you refill your prescription. There may be new information. This leaflet does not take the place of talking with your doctor about your condition or treatment.

Important information: Taclonex Scalp® Topical Suspension is for use on the scalp only (topical use only). Do not use Taclonex Scalp® Topical Suspension on the face, under arms or on groin area. Do not swallow Taclonex Scalp® Topical Suspension. Another product, Taclonex® Ointment contains the same medicine that is in Taclonex Scalp® Topical Suspension and is used to treat psoriasis vulgaris of the skin. If you use both medicines to treat your psoriasis vulgaris, be sure to follow your doctor’s directions carefully so that you do not use too much of one or both of these medicines.

What is Taclonex Scalp® Topical Suspension?

Taclonex Scalp® Topical Suspension is a prescription medicine that is for use on the scalp only (a topical medicine). Taclonex Scalp® Topical Suspension is used to treat psoriasis vulgaris in adults 18 years of age and older. Taclonex Scalp® Topical Suspension is not recommended for use in children. Taclonex Scalp® Topical Suspension has not been studied in patients under the age of 18.

Who should not use Taclonex Scalp® Topical Suspension?

Do not use Taclonex Scalp® Topical Suspension if you:

- have a calcium metabolism disorder
- have one of the following types of psoriasis:
  - erythrodermic psoriasis
  - exfoliative psoriasis
  - pustular psoriasis
- have severe kidney or liver disease.

What should I tell my doctor before using Taclonex Scalp® Topical Suspension?

Tell your doctor about all of your health conditions, including if you:

- have a skin infection on your scalp. Your skin infection should be treated before you start using Taclonex Scalp® Topical Suspension
- have thin-skin (atrophy) at the site to be treated. You should not use Taclonex Scalp® Topical Suspension
- are getting phototherapy treatments (light therapy) for your psoriasis
- are pregnant or planning to become pregnant. It is not known if Taclonex Scalp® Topical Suspension can harm your unborn baby. You and your doctor will have to decide if Taclonex Scalp® Topical Suspension is right for you while pregnant
- are breastfeeding. It is not known if Taclonex Scalp® Topical Suspension passes into your milk and can harm your baby.

Tell your doctor about all the medicines you take, including prescription, and nonprescription medicines, vitamins and herbal supplements.

Taclonex Scalp® Topical Suspension and some other medicines may interact with each other. Especially tell your doctor if you use:

- other corticosteroid medicines
- other medicines for your psoriasis.

How should I use Taclonex Scalp® Topical Suspension?

- Use Taclonex Scalp® Topical Suspension exactly as prescribed by your doctor.
- Do not use more than the maximum recommended weekly amount of 100 grams of Taclonex Scalp® Topical Suspension.
- Apply Taclonex Scalp® Topical Suspension to affected areas on the scalp once daily for 2 weeks or until cleared. Treatment may be continued for up to 8 weeks. Do not use Taclonex Scalp® Topical Suspension for more than 8 weeks unless prescribed by your doctor.
- Taclonex Scalp® Topical Suspension should only be used on the scalp. Do not use Taclonex Scalp® Topical Suspension on the face, under arms or on groin area. If you accidentally get Taclonex Scalp® Topical Suspension on your face or in your eyes wash the area with water right away.
- If you forget to use Taclonex Scalp® Topical Suspension, use it as soon as you remember. Then go on as before.
- Wash your hands well after using Taclonex Scalp® Topical Suspension.
- Do not wash your hair right after applying Taclonex Scalp® Topical Suspension. The medicine will not work as well to treat your psoriasis.

Using Taclonex Scalp® Topical Suspension:

- Do not bandage or tightly cover or wrap the treated skin area.
- Do not apply Taclonex Scalp® Topical Suspension in the 12 hours before or after any chemical treatments to your hair. Since hair treatments may involve strong chemicals, talk with your doctor first.
- Shake the bottle before use.

Remove the cap and apply Taclonex Scalp® Topical Suspension one time each day to the areas of your scalp affected by psoriasis, using the following steps (See the figures below).

What should I avoid while using Taclonex Scalp® Topical Suspension?

Avoid spending a long time in sunlight. Avoid tanning booths and sun lamps. Use sunscreen and wear a hat if you have to be in sunlight. Talk to your doctor if you get a sunburn.

What are the possible side effects of Taclonex Scalp® Topical Suspension?

Taclonex Scalp® Topical Suspension may cause serious side effects.

Serious side effects are more likely to happen if you use too much Taclonex Scalp® Topical Suspension, use it for too long, or use it with other topical medicines that contain corticosteroids, calcipotriene, or certain other ingredients. Check with your health care professional before using other topical medicines. Taclonex Scalp® Topical Suspension can pass through your skin and be absorbed into the body.

Serious side effects may include:

- too much calcium in your blood
- adrenal gland problems

Your doctor may do special blood and urine tests to check your calcium levels and adrenal gland function while you are using Taclonex Scalp® Topical Suspension.

Other side effects include:

- itching
- inflamed hair pores (folliculitis)
- skin pain or irritation
- skin burning
- redness of the skin
- worsening of psoriasis

Call your doctor about any side effect that bothers you or that does not go away.

These are not all of the side effects with Taclonex Scalp® Topical Suspension. Ask your doctor or pharmacist for more information.

How should I store Taclonex Scalp® Topical Suspension?

- Store Taclonex Scalp® Topical Suspension between 68-77°F (20-25°C). Do not refrigerate.
- Keep the bottle in the carton when not in use.
- Taclonex Scalp® Topical Suspension has an expiration date (exp.) marked on the bottom of the bottle. Do not use the topical suspension after this date.
- Use Taclonex Scalp® Topical Suspension within three months after it has been opened. After three months, safely throw away the bottle with any leftover Taclonex Scalp® Topical Suspension. If you need to keep using Taclonex Scalp® Topical Suspension or begin using it again, use a new bottle.
- Keep Taclonex Scalp® Topical Suspension and all medicines out of the reach of children.

General information about Taclonex Scalp® Topical Suspension.

Medicines are sometimes prescribed for conditions that are not mentioned in patient information leaflets. Do not use Taclonex Scalp® Topical Suspension for a condition for which it was not prescribed. Do not give your Taclonex Scalp® Topical Suspension to other people, even if they have the same symptoms you have. It may harm them.

This leaflet summarizes the most important information about Taclonex Scalp® Topical Suspension. If you would like more information, talk with your doctor. You can ask your doctor or pharmacist for information about Taclonex Scalp® Topical Suspension that is written for health professionals. For more information, please visit www.taclonex.com or call 1-877-494-4536.

What are the ingredients in Taclonex Scalp® Topical Suspension?

Active ingredients: calcipotriene hydrate, betamethasone dipropionate.

Inactive ingredients: hydrogenated castor oil, PPG-15 stearyl ether and mineral oil.

Manufactured by:

LEO Pharmaceutical Products Ltd.,
Ballerup, Denmark

LEO®

Distributed by:

LEO Pharma Inc.
1 Sylvan Way, Parsippany, NJ 07054, USA
1-877-494-4536

U.S. Patent Nos. RE39,706 E, 6,753,013 and 6,787,529.

024580-00

December 2009

Relabeling of "Additional Barcode" label by:

Physicians Total Care, Inc.
Tulsa, Oklahoma 74146

PRINCIPAL DISPLAY PANEL

Rx only

TACLONEX SCALP®
(calcipotriene 0.005% and betamethasone dipropionate 0.064%) Topical Suspension

For Topical Use Only

Net Wt. 60 g

Each gram contains 52.18 mcg of calcipotriene hydrate (equivalent to 50 mcg of calcipotriene) and 0.643 mg of betamethasone dipropionate (equivalent to 0.5 mg of betamethasone) in a base of hydrogenated castor oil, PPG-15 stearyl ether and mineral oil.

Store Taclonex Scalp® Topical Suspension between 20-25°C (68-77°F). Excursions permitted between 15-30°C (59-86°F). Do not refrigerate. Keep the bottle in the outer carton when not in use. Shake before use.

Discard product three months after opening.

Keep out of the reach of children.

Usual dosage: Apply once daily, or as directed by physician. See insert for complete information.